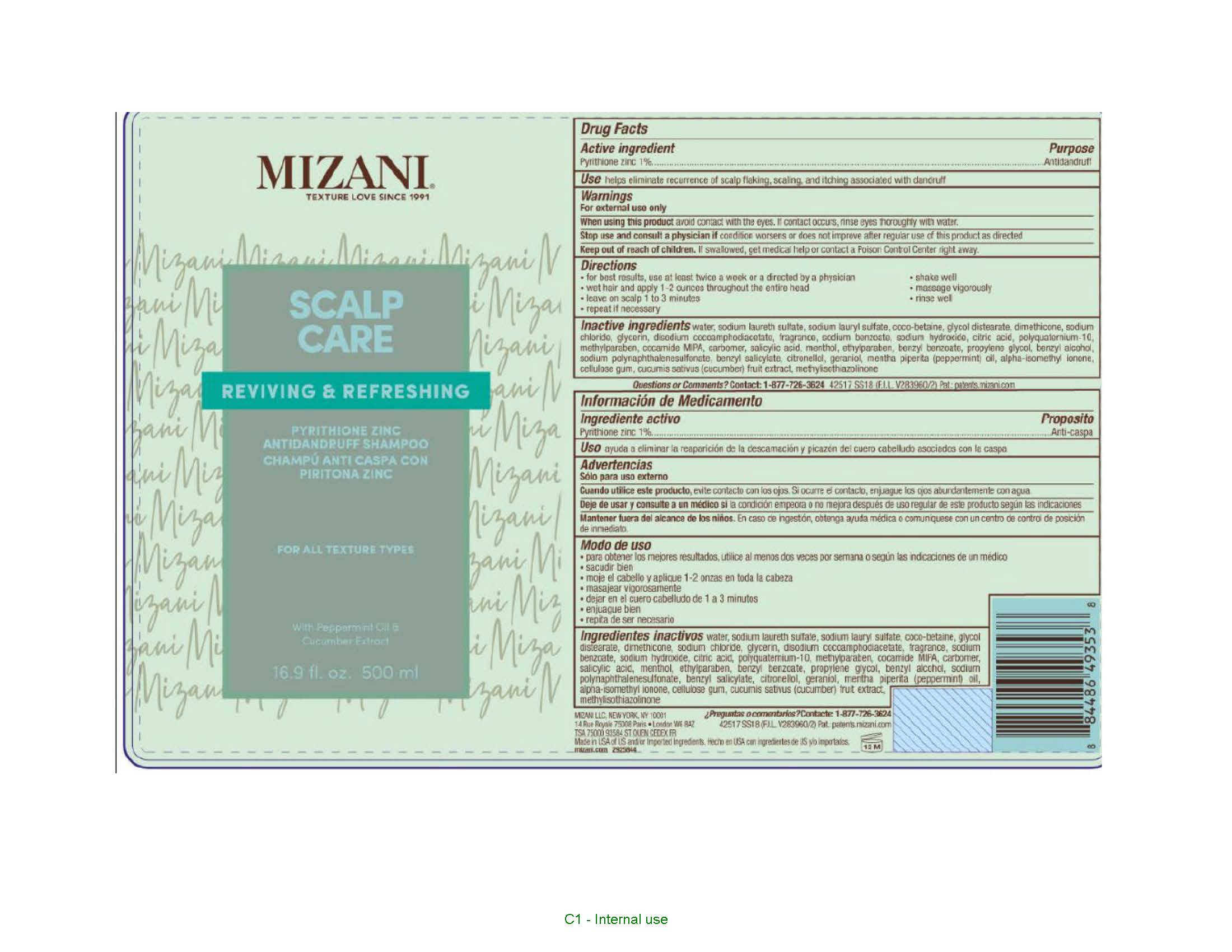 DRUG LABEL: Mizani Scalp Care Antidandruff
NDC: 49967-388 | Form: SHAMPOO
Manufacturer: L'Oreal USA Products Inc
Category: otc | Type: HUMAN OTC DRUG LABEL
Date: 20231211

ACTIVE INGREDIENTS: PYRITHIONE ZINC 10 mg/1 mL
INACTIVE INGREDIENTS: WATER; SODIUM LAURETH SULFATE; SODIUM LAURYL SULFATE; COCO-BETAINE; GLYCOL DISTEARATE; DIMETHICONE; SODIUM CHLORIDE; GLYCERIN; DISODIUM COCOAMPHODIACETATE; SODIUM BENZOATE; SODIUM HYDROXIDE; CITRIC ACID MONOHYDRATE; POLYQUATERNIUM-10 (1000 MPA.S AT 2%); METHYLPARABEN; COCO MONOISOPROPANOLAMIDE; CARBOMER HOMOPOLYMER, UNSPECIFIED TYPE; SALICYLIC ACID; MENTHOL; ETHYLPARABEN; BENZYL BENZOATE; PROPYLENE GLYCOL; BENZYL ALCOHOL; BENZYL SALICYLATE; .BETA.-CITRONELLOL, (R)-; GERANIOL; PEPPERMINT OIL; ISOMETHYL-.ALPHA.-IONONE; CARBOXYMETHYLCELLULOSE SODIUM, UNSPECIFIED; CUCUMBER; METHYLISOTHIAZOLINONE

Drug Facts

Active ingredient

Pyrithione zinc 1%

Purpose

Antidandruff

Use

helps eliminate recurrence of scalp flaking, scaling, and itching associated with dandruff

Warnings

For external use only

When using this product

do not getinto eyes. If contact occurs, rinse eyes thoroughly with water.

Stop use and consult a physician if

condition worsents or does not improve after regular use

Keep out of reach of children.

If swallowed, get medical help or contact a Poison Control Center right away.

Directions

• for best results use at least twice a week or as directed by a physician
• shake well
• wet hair and apply 1 - 2 ounces throughout entire head
• massage vigorously
• leave on scalp 1 to 3 minutes
• rinse well
• repeat if necessary

Inactive ingredients

water, sodium laureth sulfate, sodium lauryl sulfate, coco-betaine, glycol distearate, dimethicone, sodium chloride, glycerin, disodium cocoamphodiacetate, fragrance, sodium benzoate, sodium hydroxide, citric acid, polyquaternium-10, methylparaben, cocamide MIPA, carbomer, salicylic acid, menthol, ethylparaben, benzyl benzoate, propylene glycol, benzyl alcohol, sodium polynaphthalenesulfonate, benzyl salicylate, citronellol, geraniol, mentha piperita (peppermint) oil, alpha-isomethyl ionone, cellulose gum, cucumis sativus (cucumber) fruit extract, methylisothiazolinone